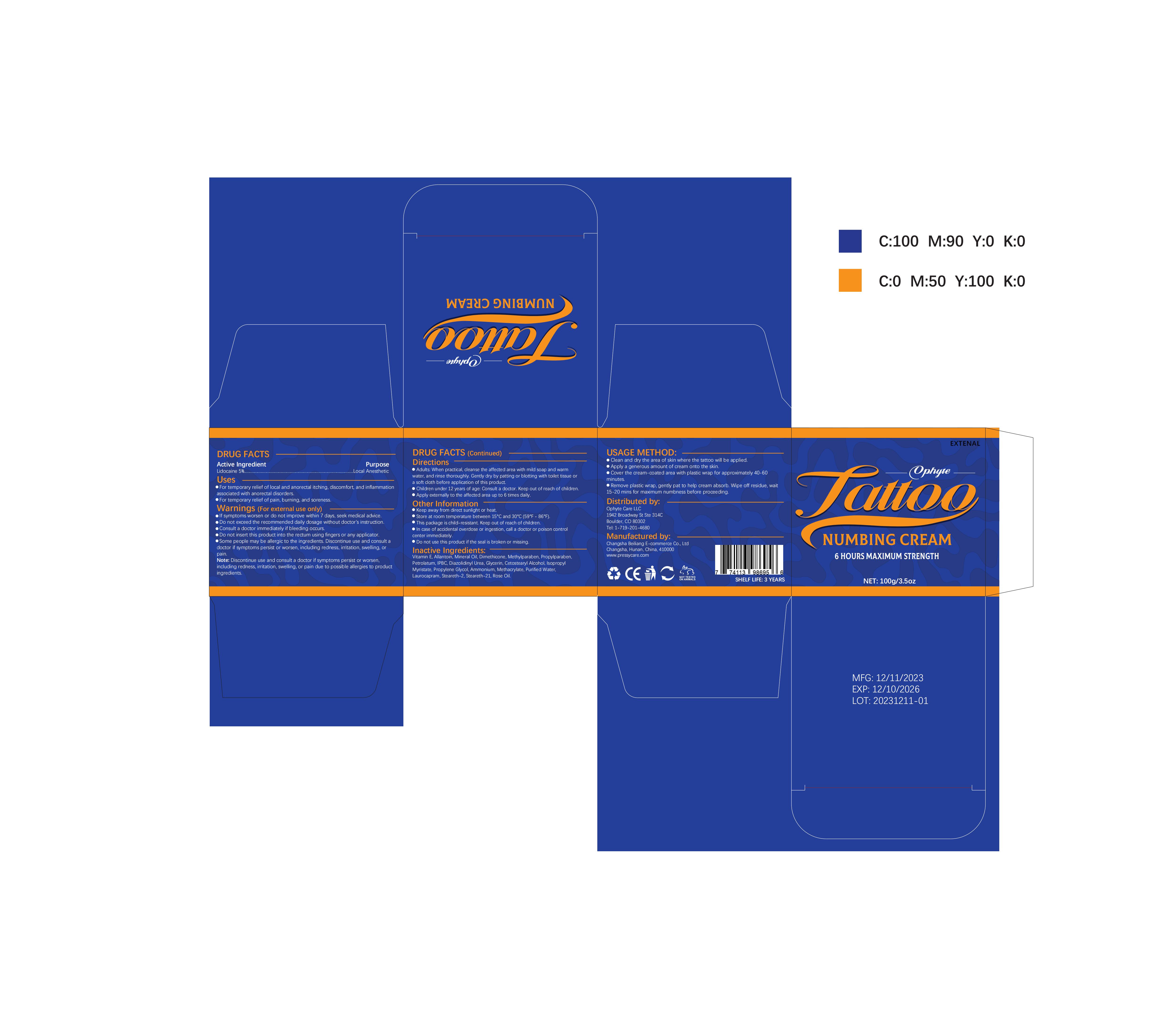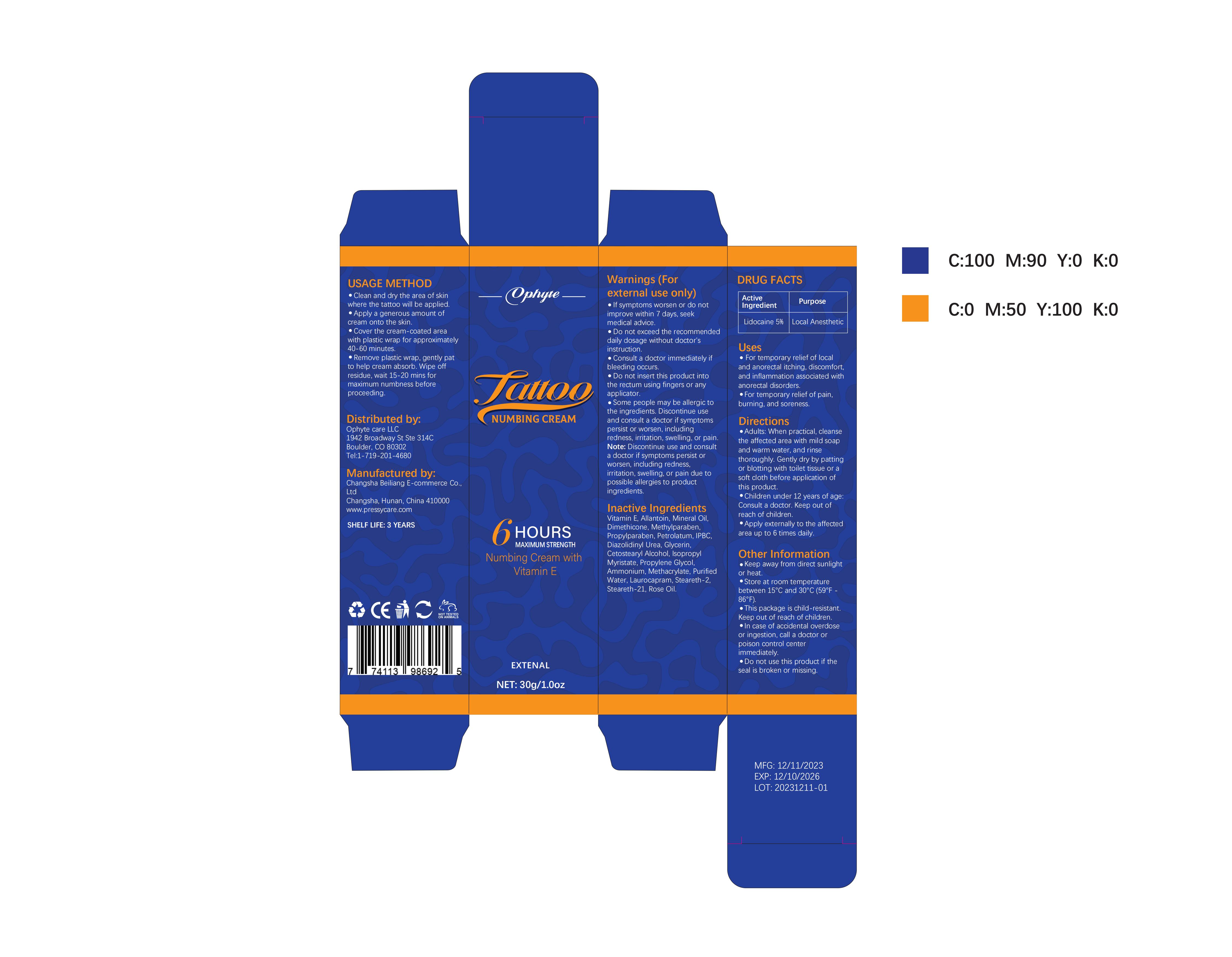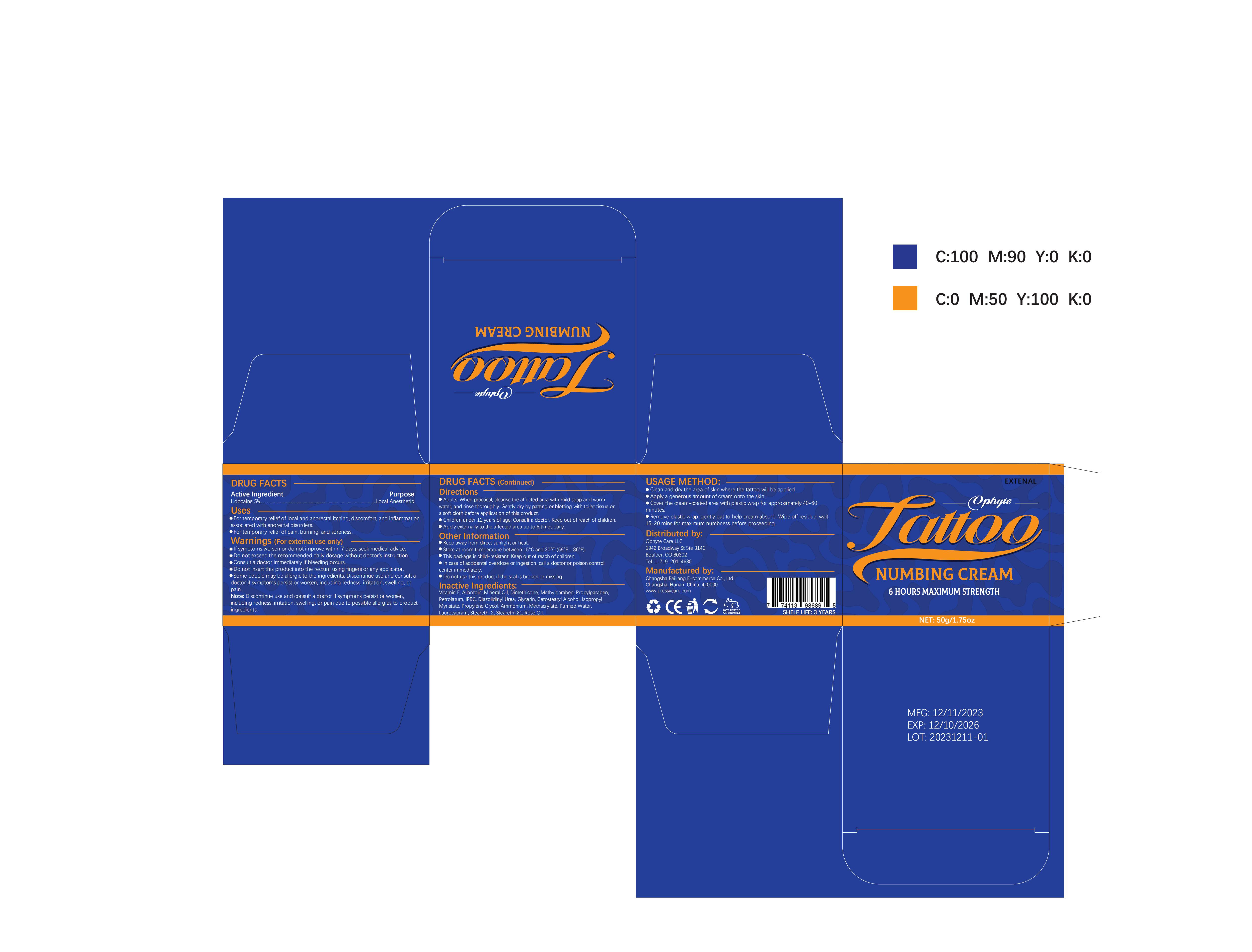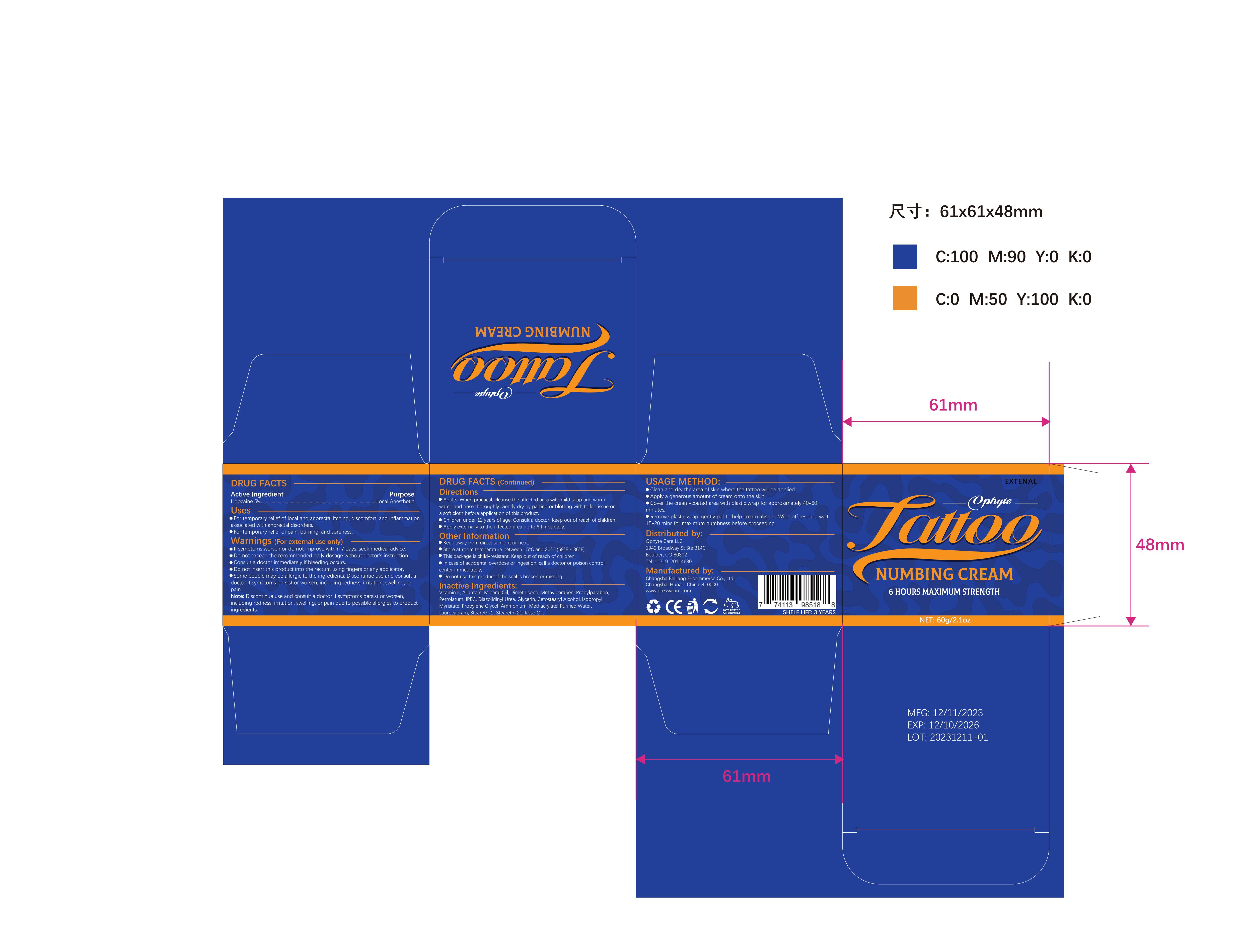 DRUG LABEL: Ophyte Tattoo Numbing Cream
NDC: 83887-002 | Form: CREAM
Manufacturer: Changsha Beiliang E-commerce Co., Ltd
Category: otc | Type: HUMAN OTC DRUG LABEL
Date: 20231223

ACTIVE INGREDIENTS: LIDOCAINE 5 g/100 g
INACTIVE INGREDIENTS: PROPYLENE GLYCOL; IODOPROPYNYL BUTYLCARBAMATE; DIAZOLIDINYL UREA; ALLANTOIN; GLYCERIN; ROSE OIL; DIMETHICONE; ISOPROPYL MYRISTATE; METHYLPARABEN; AMMONIUM METHACRYLATE; STEARETH-2; MINERAL OIL; PROPYLPARABEN; PETROLATUM; CETOSTEARYL ALCOHOL; LAUROCAPRAM; .ALPHA.-TOCOPHEROL; WATER; STEARETH-21

83887-002

Active Ingredient

Lidocaine 5%

Purpose

Local Anesthetic

Use

For temporary relief of local and anorectal itching, discomfort, and inflammation associated with anorectal disorders.
For temporary relief of pain, burning, and soreness.

Warnings

lf symptoms worsen or do notimprove within 7 days, seek medicaadvice.
Do not exceed the recommendeodaily dosage without doctor's
instruction.
Consult a doctor immediately if bleeding occurs.
Do not insert this product into the rectum using fingers or any applicator.
Some people may be allergic to the ingredients.Discontinue use and consult a doctor if symptoms persist or worsen,including redness,
irritation, swelling, or pain.
Note: Discontinue use and consult a
doctor if symptoms persist or
worsen, including redness, irritation.
swelling, or pain due to possible
allergies to product ingredients

Do not use

Some people may be allergic tothe ingredients. Discontinue use andconsult a doctor if symptoms persistor worsen,including rednessirritation,swelling,or pain.

When Using

If symptoms worsen or do not improve within 7 days, seek medicaladvice.Do not exceed the recommended daily dosage without doctor'sinstruction.Consult a doctor immediately if bleeding occurs.
Do not insert this product into the rectum using fingers or any applicator.
Some people may be allergic to the ingredients. Discontinue use and consult a doctor if symptoms persistor worsen,including redness,irritation,swelling,or pain.

Stop Use

Discontinue use and consult adoctor if symptoms persist orworsen, including redness, irritation,swelling, or pain due to possibleallergies to product ingredients.

Ask Doctor

Discontinue use and consult a doctor if symptoms persist or worsen, including redness, irritation. swelling, or pain due to possible
allergies to product ingredients

Keep Oot Of Reach Of Children

This package is child-resistant.Keep out of reach of children

Directions

Adults: When practical, cleanse theaffected area with mild soap andwarm water, and rinse thoroughlyGently dry by patting or blotting withtoilet tissue or a soft cloth beforeapplication of this product.

Other information

Keep away from direct sunlight orheat.
Store at room temperaturebetween 15°C and 30°C(59°F-86°F).
This package is child-resistant.Keep out of reach of children. In case of accidental overdose oringestion, call a doctor or poisoncontrol center immediately. Do not use this product if the sealis broken or missing.

Inactive ingredients

Vitamin E Allantoin, Mineral Oil.Dimethicone,MethylparabenPropylparaben, Petrolatum, IPBCDiazolidinyl Urea, Glycerin,Cetostearyl Alcohol, IsopropylMyristate, Propylene Glycol,Ammonium,Methacrylate, PurifiedWater, Laurocapram, Steareth-2.Steareth-21 Rose Oil